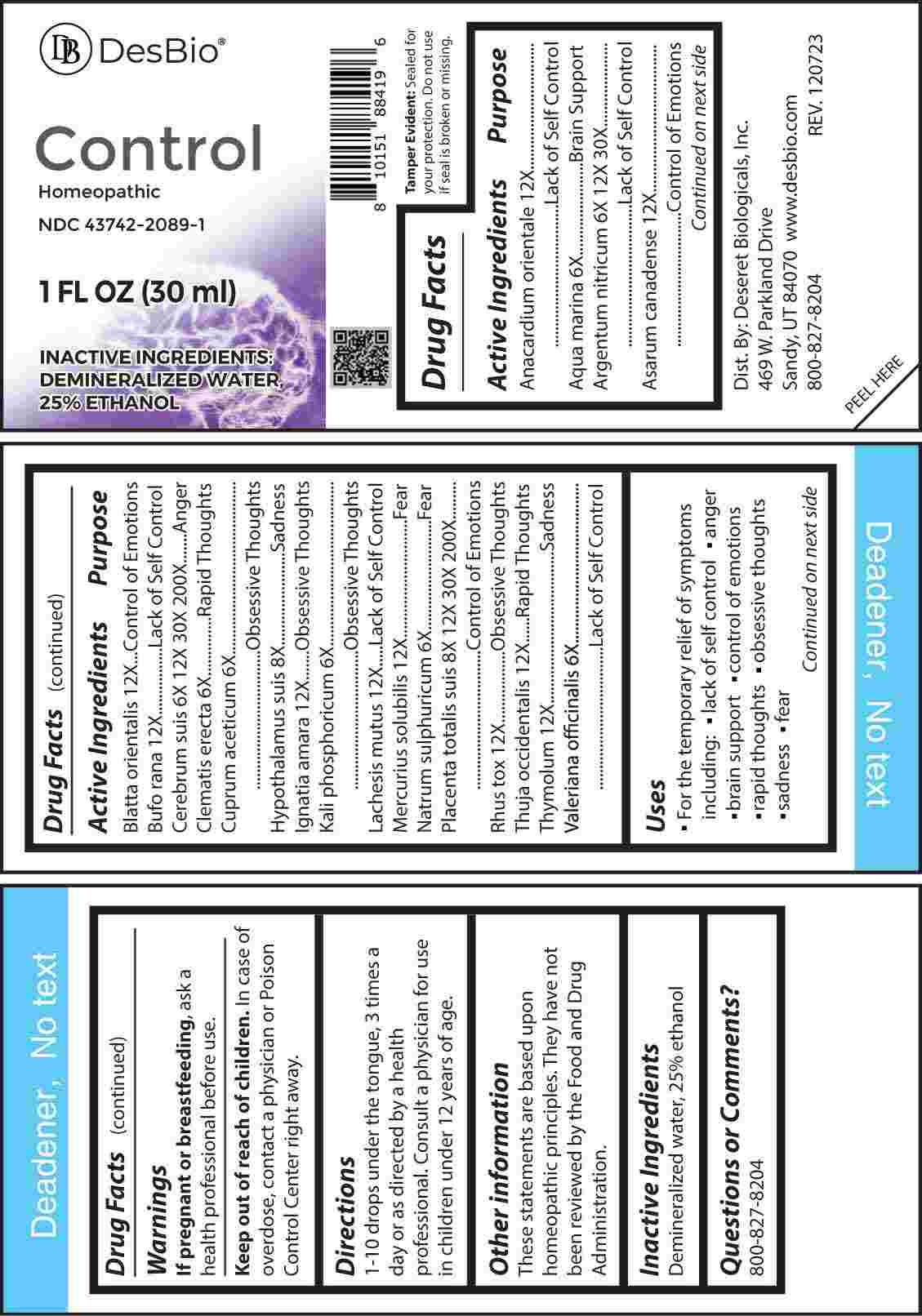 DRUG LABEL: Control
NDC: 43742-2089 | Form: LIQUID
Manufacturer: Deseret Biologicals, Inc.
Category: homeopathic | Type: HUMAN OTC DRUG LABEL
Date: 20240325

ACTIVE INGREDIENTS: SEMECARPUS ANACARDIUM JUICE 12 [hp_X]/1 mL; SODIUM CHLORIDE 6 [hp_X]/1 mL; SILVER NITRATE 6 [hp_X]/1 mL; ASARUM CANADENSE ROOT 12 [hp_X]/1 mL; BLATTA ORIENTALIS 12 [hp_X]/1 mL; BUFO BUFO CUTANEOUS GLAND 12 [hp_X]/1 mL; SUS SCROFA CEREBRUM 6 [hp_X]/1 mL; CLEMATIS RECTA FLOWERING TOP 6 [hp_X]/1 mL; CUPRIC ACETATE 6 [hp_X]/1 mL; SUS SCROFA HYPOTHALAMUS 8 [hp_X]/1 mL; STRYCHNOS IGNATII SEED 12 [hp_X]/1 mL; DIBASIC POTASSIUM PHOSPHATE 6 [hp_X]/1 mL; LACHESIS MUTA VENOM 12 [hp_X]/1 mL; MERCURIUS SOLUBILIS 12 [hp_X]/1 mL; SODIUM SULFATE 6 [hp_X]/1 mL; SUS SCROFA PLACENTA 8 [hp_X]/1 mL; TOXICODENDRON PUBESCENS LEAF 12 [hp_X]/1 mL; THUJA OCCIDENTALIS LEAFY TWIG 12 [hp_X]/1 mL; THYMOL 12 [hp_X]/1 mL; VALERIAN 6 [hp_X]/1 mL
INACTIVE INGREDIENTS: WATER; ALCOHOL

DRUG FACTS:

ACTIVE INGREDIENTS:

Anacardium Orientale 12X, Aqua Marina 6X, Argentum Nitricum 6X, 12X, 30X, Asarum Canadense 12X, Blatta Orientalis 12X, Bufo Rana 12X, Cerebrum Suis 6X, 12X, 30X, 200X, Clematis Erecta 6X, Cuprum Aceticum 6X, Hypothalamus Suis 8X, Ignatia Amara 12X, Kali Phosphoricum 6X, Lachesis Mutus 12X, Mercurius Solubilis 12X, Natrum Sulphuricum 6X, Placenta Totalis Suis 8X, 12X, 30X, 200X, Rhus Tox 12X, Thuja Occidentalis 12X, Thymolum 12X, Valeriana Officinalis 6X.

PURPOSE:

Anacardium Orientale – Lack of Self Control, Aqua Marina – Brain Support, Argentum Nitricum – Lack of Self Control, Asarum Canadense – Control of Emotions, Blatta Orientalis – Control of Emotions, Bufo Rana – Lack of Self Control, Cerebrum Suis - Anger, Clematis Erecta – Rapid Thoughts, Cuprum Aceticum – Obsessive Thoughts, Hypothalamus Suis - Sadness, Ignatia Amara – Obsessive Thoughts, Kali Phosphoricum -Obsessive Thoughts, Lachesis Mutus – Lack of Self Control, Mercurius Solubilis - Fear, Natrum Sulphuricum -Fear, Placenta Totalis Suis – Control of Emotions, Rhus Tox – Obsessive Thoughts, Thuja Occidentalis – Rapid Thoughts, Thymolum - Sadness, Valeriana Officinalis – Lack of Self Control.

USES:

• For the temporary relief of symptoms including:

• lack of self control • anger • brain support

• control of emotions • rapid thoughts

• obsessive thoughts • sadness • fear

These statements are based upon homeopathic principles. They have not been reviewed by the Food and Drug Administration.

WARNINGS:

If pregnant or breast-feeding, ask a health professional before use.

Keep out of reach of children. In case of overdose, contact a physician or Poison Control Center right away.

Tamper Evident: Sealed for your protection. Do not use if seal is broken or missing.

KEEP OUT OF REACH OF CHILDREN:

In case of overdose, contact a physician or Poison Control Center right away.

DIRECTIONS:

1-10 drops under the tongue, 3 times a day or as directed by a health professional. Consult a physician for use in children under 12 years of age.

INACTIVE INGREDIENTS:

Demineralized water, 25% ethanol

QUESTIONS:

Dist. By: Deseret Biologicals, Inc.
469 W. Parkland Drive
Sandy, UT 84070

www.desbio.com

800-827-8204

PACKAGE LABEL DISPLAY:

DesBio

Control

Homeopathic
NDC 43742-2089-1
1 FL OZ (30 ml)